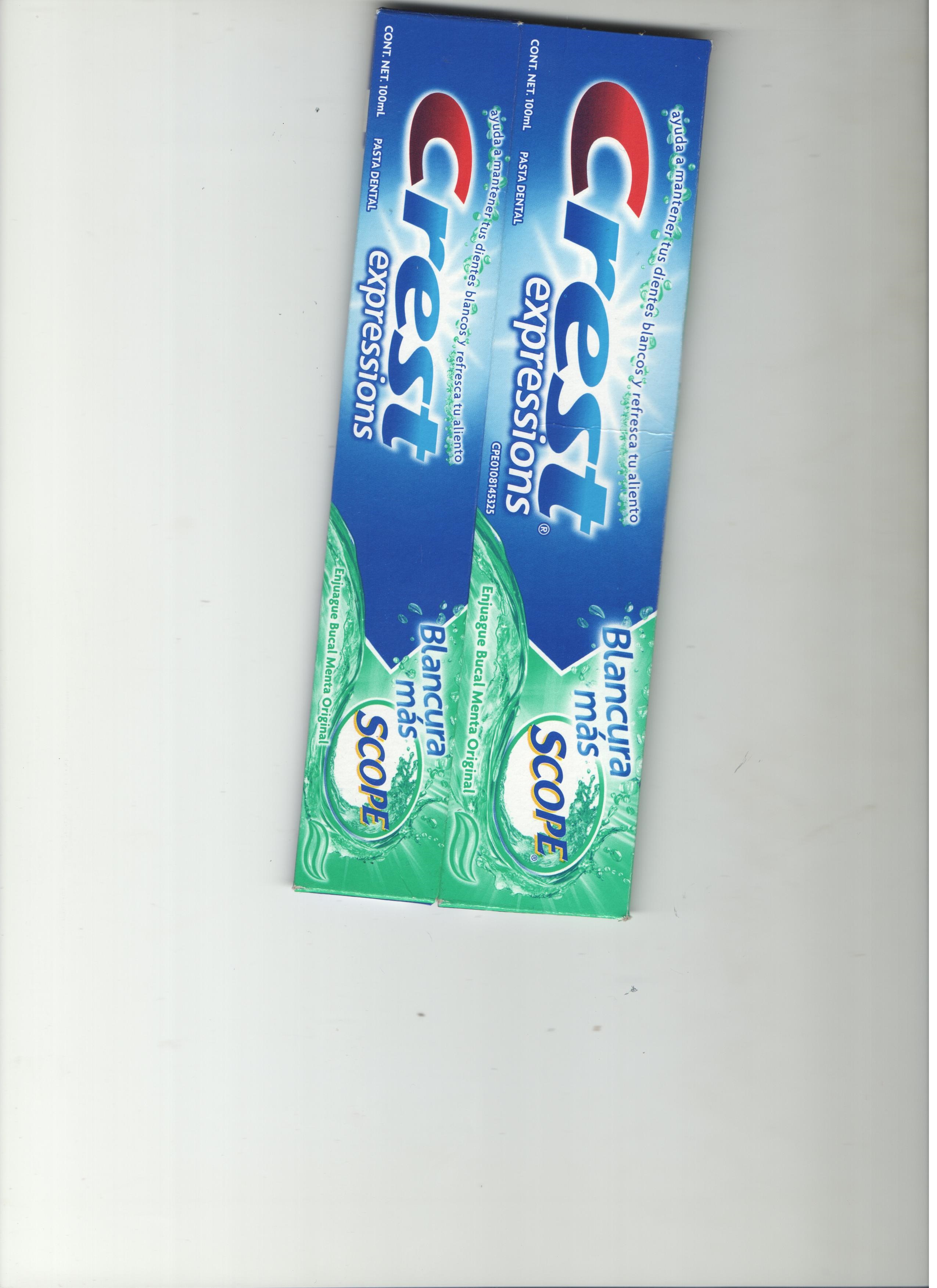 DRUG LABEL: Crest Expressions Scope
NDC: 69772-820 | Form: PASTE, DENTIFRICE
Manufacturer: Teresa Cecena DBA Genesis Imports
Category: otc | Type: HUMAN OTC DRUG LABEL
Date: 20160128

ACTIVE INGREDIENTS: SODIUM FLUORIDE 243 mg/1 g
INACTIVE INGREDIENTS: SORBITOL; WATER; SODIUM HYDROXIDE; SACCHARIN SODIUM DIHYDRATE; GLYCERIN; CARBOXYMETHYLCELLULOSE SODIUM; POLYSORBATE 80; XANTHAN GUM; TITANIUM DIOXIDE; FD&C YELLOW NO. 5; SODIUM BENZOATE; CETYLPYRIDINIUM CHLORIDE; BENZOIC ACID; FD&C BLUE NO. 1; HYDRATED SILICA; SODIUM ACID PYROPHOSPHATE; SODIUM LAURYL SULFATE; ALCOHOL

ACTIVE INGREDIENT

Sodium Fluoride

PURPOSE

Anticavity toothpaste

WARNINGS

kEEP OUT OF REACH OF CHILDREN UNDER 6 YRS OF AGE.IF MORE THAT USED FOR BRUSHING IS ACCIDENTALLY SWALLOWED, GET MEDICAL HELP OR CONTACT A POISON CONTROL VENTER RIGHT AWAY.

DIRECTIONS

- Adults and children 2 yrs. & older; brush teeth thoroughly after meals or at least twice a day or use as directed a dentist
- do not swallow

to minimize swallowing use a pea-sized amount in children under 6

supervise children's brushing until good habits are established

- children under 2 yrs, ask a dentist

INACTIVE INGREDIENT

sorbitol,water,hydrated silica,disodium pyrophosphate, sodium lauryl sulfate, flavor, sodium hydroxide, alcohol, xanthan gum, sodium saccharin , glycerin, carbomer, cellulose gum, polysorbate 80, sodium benzoate, cethylpyridinium chloride, benzoic acid, titanium dioxide, blue 1, yellow 5

QUESTIONS?

1-800-492-7378

KEEP OUT OF REACH OF CHILDREN UNDER 6 YEARS

DOSAGE AND ADMINISTRATION

DIRECTION

Adults and childreen 2 yrs and older ; brush teeth thoroughly after meals or at least twice a day or use as directed by a dentist